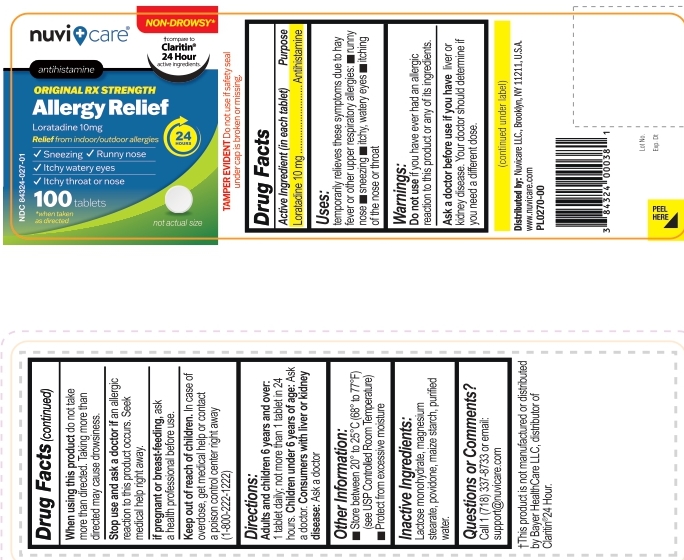 DRUG LABEL: Nuvicare-Allergy Relief Loratadine Tablets, 10 mg
NDC: 84324-027 | Form: TABLET
Manufacturer: NUVICARE LLC
Category: otc | Type: HUMAN OTC DRUG LABEL
Date: 20250701

ACTIVE INGREDIENTS: LORATADINE 10 mg/1 1
INACTIVE INGREDIENTS: LACTOSE MONOHYDRATE; MAGNESIUM STEARATE; povidone; STARCH, CORN

Nuvicare-Allergy Relief Loratadine Tablets, 10 mg

Active Ingredient (in each tablet)

Loratadine, 10 mg

Purpose

Antihistamine

Uses

Temporarily relieves these symptoms due to hay fever or other respiratory allergies:

- runny nose
- sneezing
- itchy, watery eyes
- itching of the nose or throat

Warnings

Do not use if you ever have had an allergic reaction to this product or any of its ingredients.

Ask a doctor before use if you have liver or kidney disease. Your doctor should determine if you need a different dose.

When using this product do not take more than directed. Taking more than directed may cause drowsiness.

Stop use and ask a doctor if an allergic reaction to this product occurs. Seek medical help right away.

PREGNANCY OR BREAST FEEDING

If pregnanct or breast-feeding, ask a health professional before use.

Keep out of reach of children. In case of overdose, get medical help or contact a poison control center right away (1-800-222-1222)

Directions

Adults and children 6 years and over: 1 tablet daily; not more than 1 tablet in 24 hours.
Children under 6 years of age: Ask a doctor.
Consumers with liver or kidney disease: Ask a doctor

Other Information

- Store between 20° to 25°C (68° to 77°F) (see USP Controlled Room Temperature)
- Protect from excessive moisture

Inactive ingredients

Lactose monohydrate, magnesium stearate, povidone, maize starch, purified water.

Questions or comments?

Call 1(718) 337-8733 or email: support@nuvicare.com